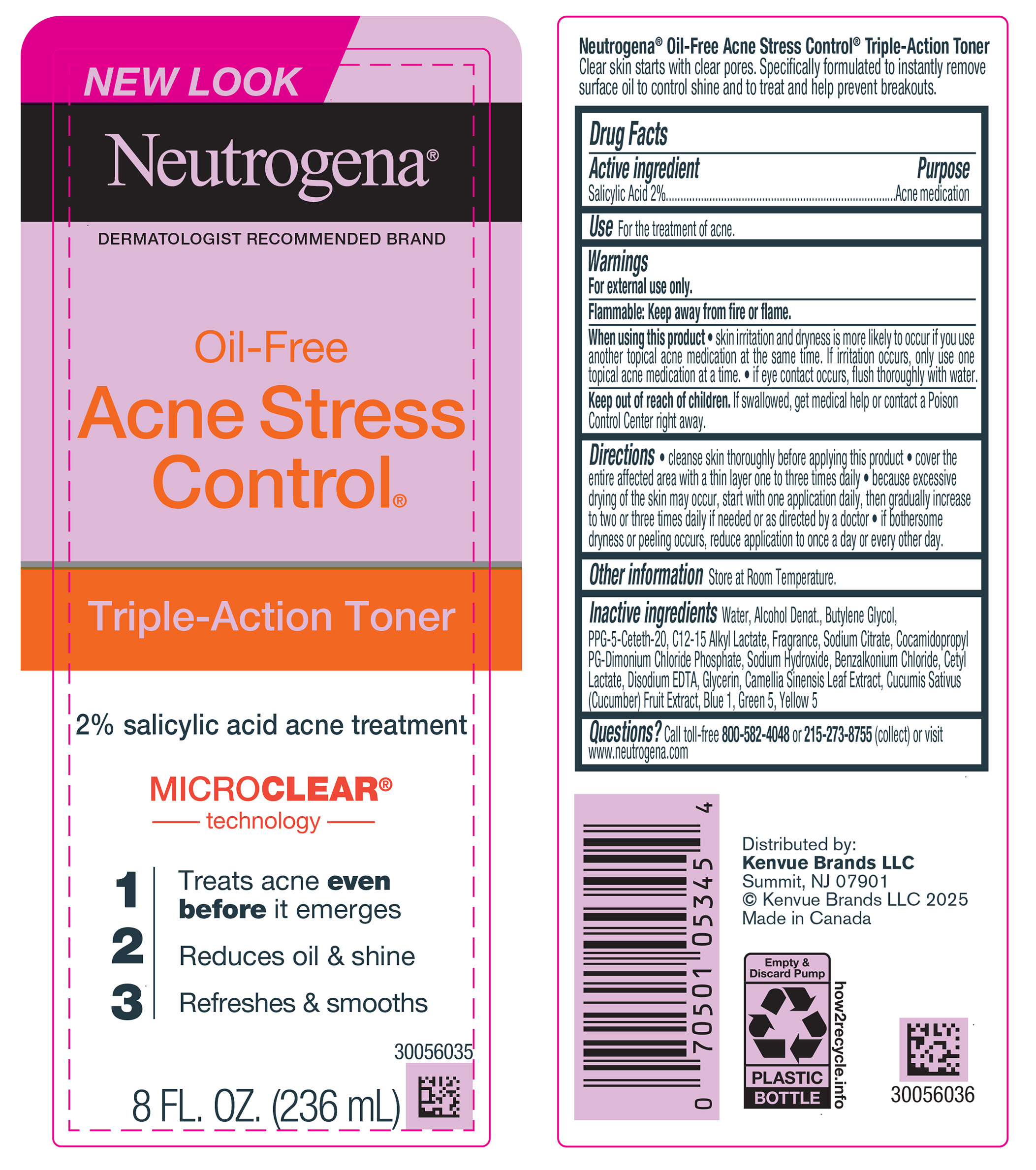 DRUG LABEL: Neutrogena Oil Free Acne Stress Control Triple Action Toner
NDC: 69968-0925 | Form: LIQUID
Manufacturer: Kenvue Brands LLC
Category: otc | Type: HUMAN OTC DRUG LABEL
Date: 20250529

ACTIVE INGREDIENTS: SALICYLIC ACID 20 mg/1 mL
INACTIVE INGREDIENTS: WATER; ALCOHOL; BUTYLENE GLYCOL; PPG-5-CETETH-20; C12-15 ALKYL LACTATE; SODIUM CITRATE, UNSPECIFIED FORM; COCAMIDOPROPYL PROPYLENE GLYCOL-DIMONIUM CHLORIDE PHOSPHATE; SODIUM HYDROXIDE; BENZALKONIUM CHLORIDE; CETYL LACTATE; EDETATE DISODIUM; GLYCERIN; CUCUMIS SATIVUS (CUCUMBER) FRUIT; BLUE 1; GREEN 5; YELLOW 5; CAMELLIA SINENSIS LEAF

Neutrogena® Oil - Free Acne Stress Control® Triple - Action Toner

Drug Facts

Active ingredient

Salicylic Acid 2%

Purpose

Acne medication

Use

For the treatment of acne.

Warnings

For external use only.

Flammable: Keep away from fire or flame.

When using this product

- skin irritation and dryness is more likely to occur if you use another topical acne medication at the same time. If irritation occurs, only use one topical acne medication at a time.
- if eye contact occurs, flush thoroughly with water.

- Keep out of reach of children. If swallowed, get medical help or contact a Poison Control Center right away.

Directions

- cleanse skin thoroughly before applying this product
- cover the entire affected area with a thin layer one to three times daily
- because excessive drying of the skin may occur, start with one application daily, then gradually increase to two or three times daily if needed or as directed by a doctor
- if bothersome dryness or peeling occurs, reduce application to once a day or every other day.

Other information

Store at Room Temperature.

Inactive ingredients

Water, Alcohol Denat., Butylene Glycol, PPG-5-Ceteth-20, C12-15 Alkyl Lactate, Fragrance, Sodium Citrate, Cocamidopropyl

PG-Dimonium Chloride Phosphate, Sodium Hydroxide, Benzalkonium Chloride, Cetyl Lactate, Disodium EDTA, Glycerin, Camellia Sinensis Leaf Extract, Cucumis Sativus (Cucumber) Fruit Extract, Blue 1, Green 5, Yellow 5

Questions?

Call toll-free 800-582-4048 or 215-273-8755 (collect) or visit www.neutrogena.com

Distributed by:

Kenvue Brands LLC

Summit, NJ 07901

PRINCIPAL DISPLAY PANEL - 236 mL Bottle Label

NEW LOOK

Neutrogena®

DERMATOLOGIST RECOMMENDED BRAND

Oil-Free

Acne Stress

Control®

Triple-Action Toner

2% salicylic acid acne treatment

MICROCLEAR®

Technology

1 Treats acne even before it emerges

2 Reduces oil & shine

3 Refreshes & smooths

8 FL. OZ. (236 mL)